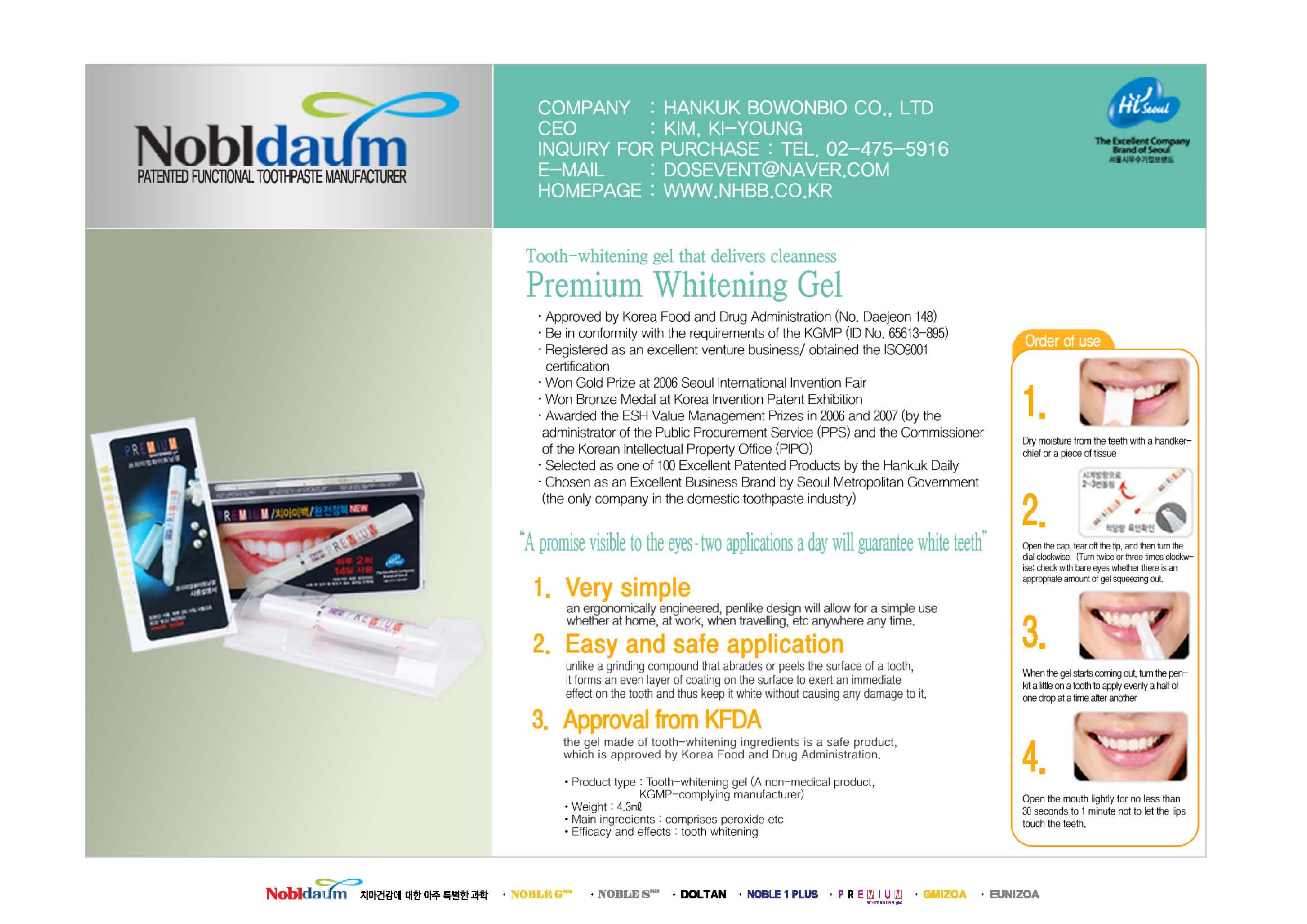 DRUG LABEL: Premium Whitening
NDC: 60319-1001 | Form: GEL, DENTIFRICE
Manufacturer: Hankuk Bowonbio Co., Ltd
Category: otc | Type: HUMAN OTC DRUG LABEL
Date: 20191203

ACTIVE INGREDIENTS: HYDROGEN PEROXIDE 35 mL/100 mL
INACTIVE INGREDIENTS: ALCOHOL; POVIDONE; SODIUM STANNATE; WATER

Drug Facts

active ingredient: hydrogen peroxide solution
<text><content
styleCode="xmChange">
</content></text>

inactive ingredient: polyvinyl alcohol, povidone, sodium stannate, purified water
<text><content
styleCode="xmChange">
</content></text>

PURPOSE

for dental care use
<text><content
styleCode="xmChange">
</content></text>

keep out of reach of the children
<text><content
styleCode="xmChange">
</content></text>

INDICATIONS AND USAGE

apply Proper Amount of the gel on the teeth.

WARNINGS

■ For tooth only.
■ Avoid contact with eyes.
■ Do not swallow. If swallowed, get medical help.

DOSAGE AND ADMINISTRATION

dry the tooth to be applied